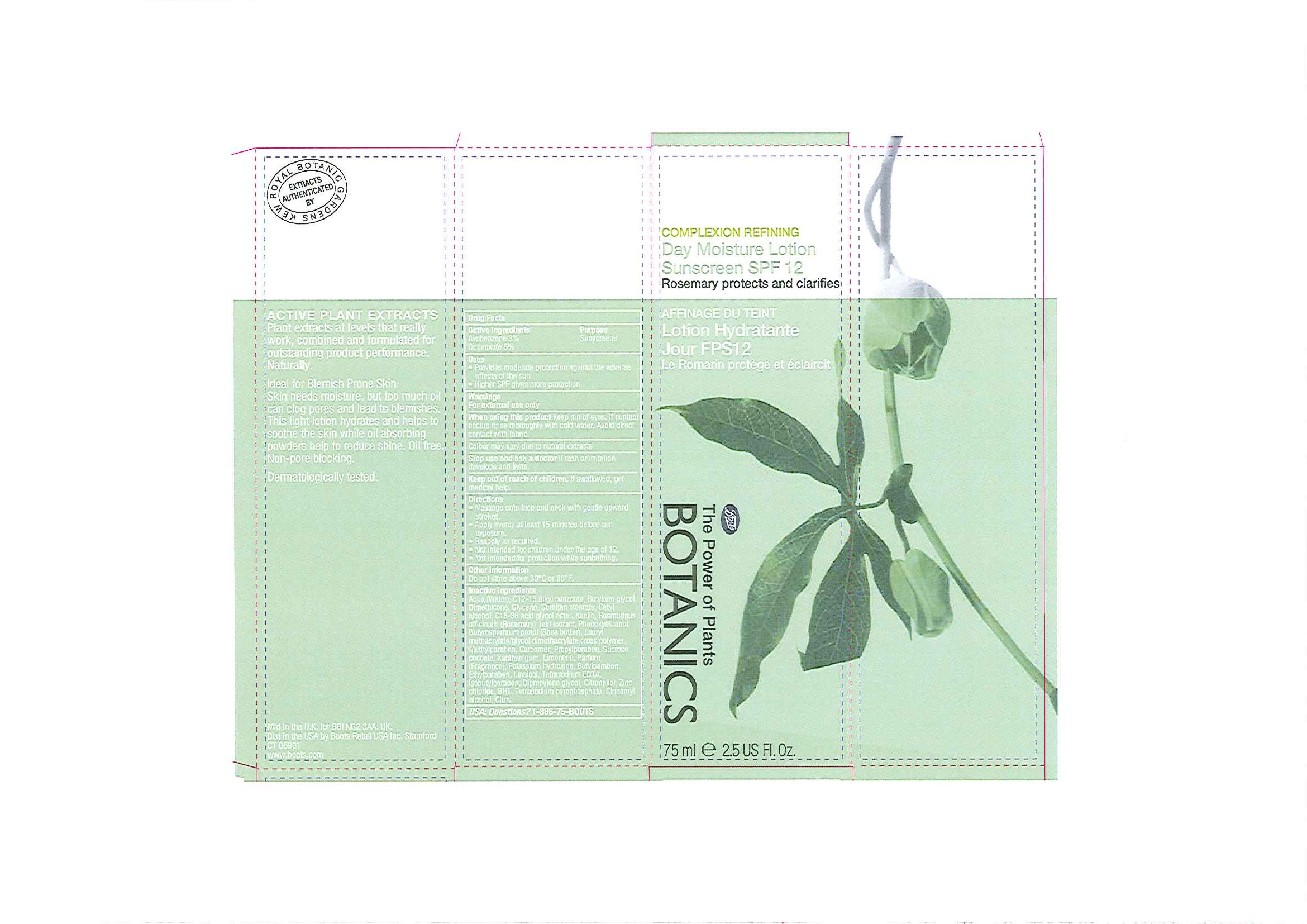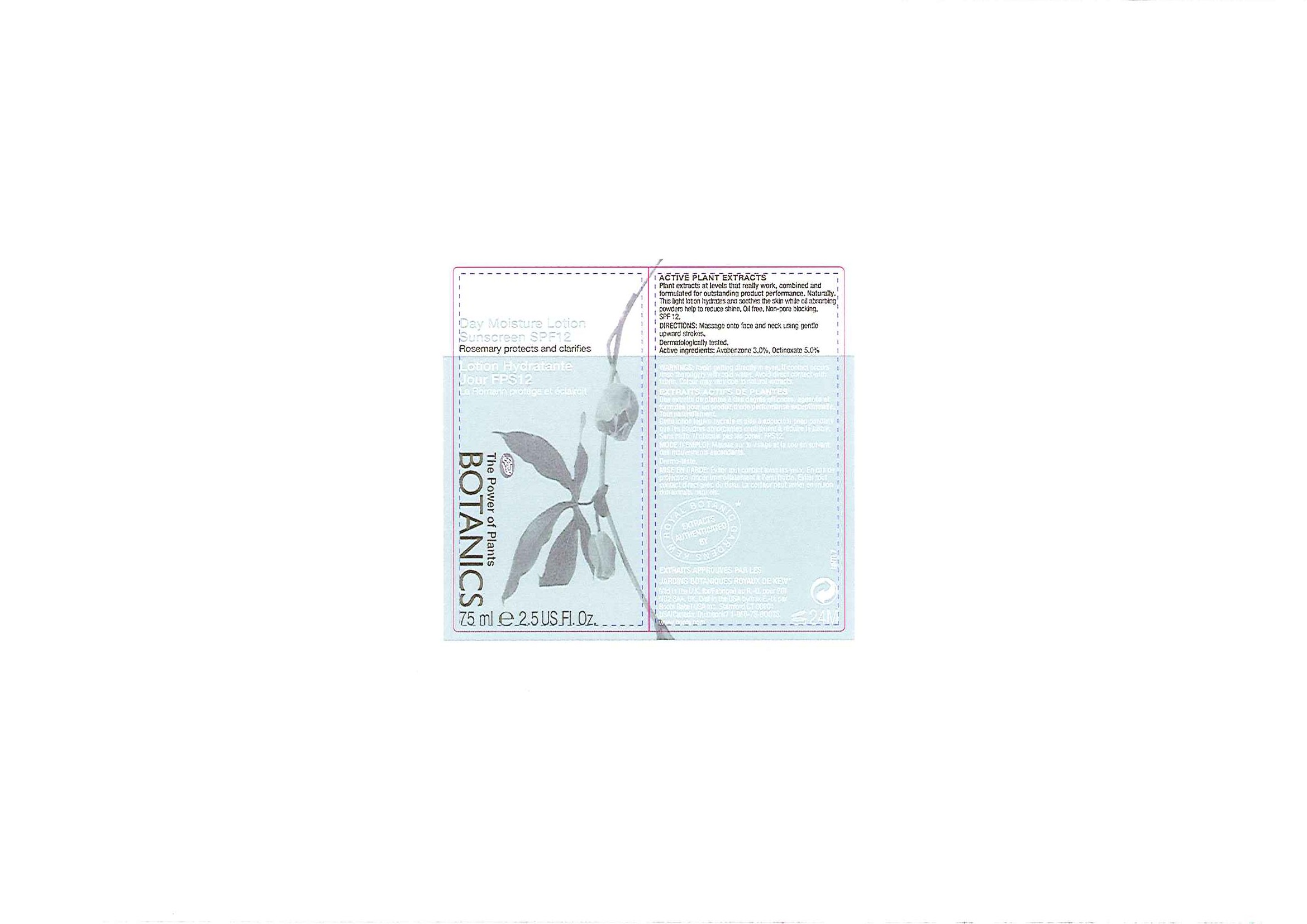 DRUG LABEL: Botanics Complexion Refining Day Moisture Sunscreen SPF 12
NDC: 11489-060 | Form: LOTION
Manufacturer: BCM Ltd
Category: otc | Type: HUMAN OTC DRUG LABEL
Date: 20101208

ACTIVE INGREDIENTS: Octinoxate 3.75 mL/75 mL; Avobenzone 2.25 mL/75 mL
INACTIVE INGREDIENTS: Water; Butylene Glycol; Dimethicone; Glycerin; Sorbitan Monostearate; Cetyl Alcohol; Kaolin; Rosemary; Phenoxyethanol; Shea Butter; Methylparaben; Carbomer Homopolymer Type C; Propylparaben; Xanthan Gum; Potassium Hydroxide; Butylparaben; Ethylparaben; Isobutylparaben; Zinc Chloride; Butylated Hydroxytoluene; Sodium Pyrophosphate

Carton and tube labelling

ACTIVE INGREDIENT

BOTANICS COMPLEXION REFINING DAY MOISTURE LOTION SUNSCREEN SPF 12

Active Ingredients Purpose

Avobenzone 3% Sunscreens

Octinoxate 5%

Uses

- Provides moderate protection against the adverse effects of the sun
- Higher SPF gives more protection

Warnings

For external use only

When using this product keep out of eyes. If contact occurs rinse thoroughly with cold water. Avoid direct contact with fabric.

HOW SUPPLIED

Colour may vary due to natural extracts

Stop use and ask a doctor if rash or irritation develops and lasts.

Keep out of reach of children. If swallowed, get medical help.

Directions

- Massage onto face and neck with gentle upward strokes.
- Apply evenly at least 15 minutes before sun exposure.
- Reapply as required.
- Not intended for children under the age of 12.
- Not intended for protection while sunbathing.

Other Information

Do not store above 30oC or 86oF.

Inactive ingredients

Aqua (Water), C12-15 alkyl benzoate, Butylene glycol, Dimethicone, Glycerin, Sorbitan stearate, Cetyl alcohol, C18-36 acid glycol ester, Kaolin, Rosmarinus officinalis (Rosemary) leaf extract, Phenoxyethanol, Butyrospermum parkii (Shea butter), Lauryl methacrylate/glycol dimethacrylate cross polymer, Methylparaben, Carbomer, Propylparaben, Sucrose cocoate, Xanthan gum, Limonene, Parfum (Fragrance), Potassium hydroxide, Butylparaben, Ethylparaben, Linalool, Tetrasodium EDTA, Isobutylparaben, Dipropylene glycol, Citronellol, Zinc chloride, BHT, Tetrasodium pyrophosphate, Cinnamyl alcohol, Citral

USA: Questions? 1-866-75-BOOTS

DESCRIPTION

ACTIVE PLANT EXTRACTS

Plant extracts at levels that really work, combined and formulated for outstanding product performance.

Naturally.

Ideal for Blemish Prone Skin

Skin needs moisture, but too much oil can clog pores and lead to blemishes. This light lotion hydrates and helps to soothe the skin while oil absorbing powders help to reduce shine.

Oil Free. Non-pore blocking.

Dermatologically tested.

PATIENT COUNSELING INFORMATION

Mfd in the U.K. for BBI NG2 3AA. UK.

Dist in the USA by Boots Retail USA Inc. Stamford CT 06901

www.boots.com

DESCRIPTION

Tube label

ACTIVE PLANT EXTRACTS

Plant extract at levels that really work, combined and formulated for outstanding product performance. Naturally.

This light lotion hydrates and soothes the skin while oil absorbing powders help to reduce shine.

Oil free. Non-pore blocking. SPF 12.

Dermatologically tested.

EXTRAITS ACTIFS DE PLANTES
Des extraits de plantes à des degrés efficaces, agencés et formulés pour un produit d'une performance exceptionnelle. Tout naturellement.
Cette lotion légère hydrate et aide à adoucir la peau pendant que les poudres absorbantes contribuent à réduire le lustre.
Sans huile. N'obstrue pas les pores. FPS 12.
Dermo-testé

INDICATIONS AND USAGE

DIRECTIONS: Massage onto face and neck using gentle upward strokes.

MODE D'EMPLOI: Massez sur le visage et le cou en suivant des mouvements ascendants.

Active ingredients: Avobenzone 3.0%, Octinoxate 5.0%

WARNINGS AND PRECAUTIONS

WARNINGS: Avoid getting directly in eyes. If contact occurs rinse thoroughly with cold water. Avoid direct contact with fabric.

MISE EN GARDE: Éviter tout contact avec les yeux. En cas de projection, rincer immédiatement à l'eau froide. Éviter tout contact direct avec du tissu.

HOW SUPPLIED

Colour may vary due to natural extracts.

La couleur peut varier en raison des extraits naturels.

PATIENT COUNSELING INFORMATION

EXTRACTS AUTHENTICATED BY ROYAL BOTANIC GARDENS KEW

EXTRAITS APPROUVES PAR LES JARDINS BOTANIQUES ROYAUX DE KEW

Mfd in the U.K. for/Fabriqué au R.-U. pour BBI NG2 3AA. UK.

Dist in the USA by/aux É.-U. par Boots Retail USA Inc. Stamford CT 06901

USA/Canada: Questions? 1-866-75-BOOTS

www.boots.com

Carton label

COMPLEXION REFINING

Day Moisture Lotion Sunscreen SPF 12

Rosemary protects and clarifies

AFFINAGE DU TEINT

Lotion Hydratante Jour FPS12

Le Romarin protège et éclaircit

BOOTS

The Power of Plants

BOTANICS

75ml e 2.5 US Fl. Oz

CR Day Moisture Lotion carton.jpg

PACKAGE LABEL

Day Moisture Lotion Sunscreen SPF 12

Rosemary protects and clarifies

Lotion Hydratante Jouse FPS12

Le Romarin protège et éclaircit

Boots

The Power of Plants

BOTANICS

75ml e 2.5 US Fl. Oz

CR Day Moisture Lotion label.jpg